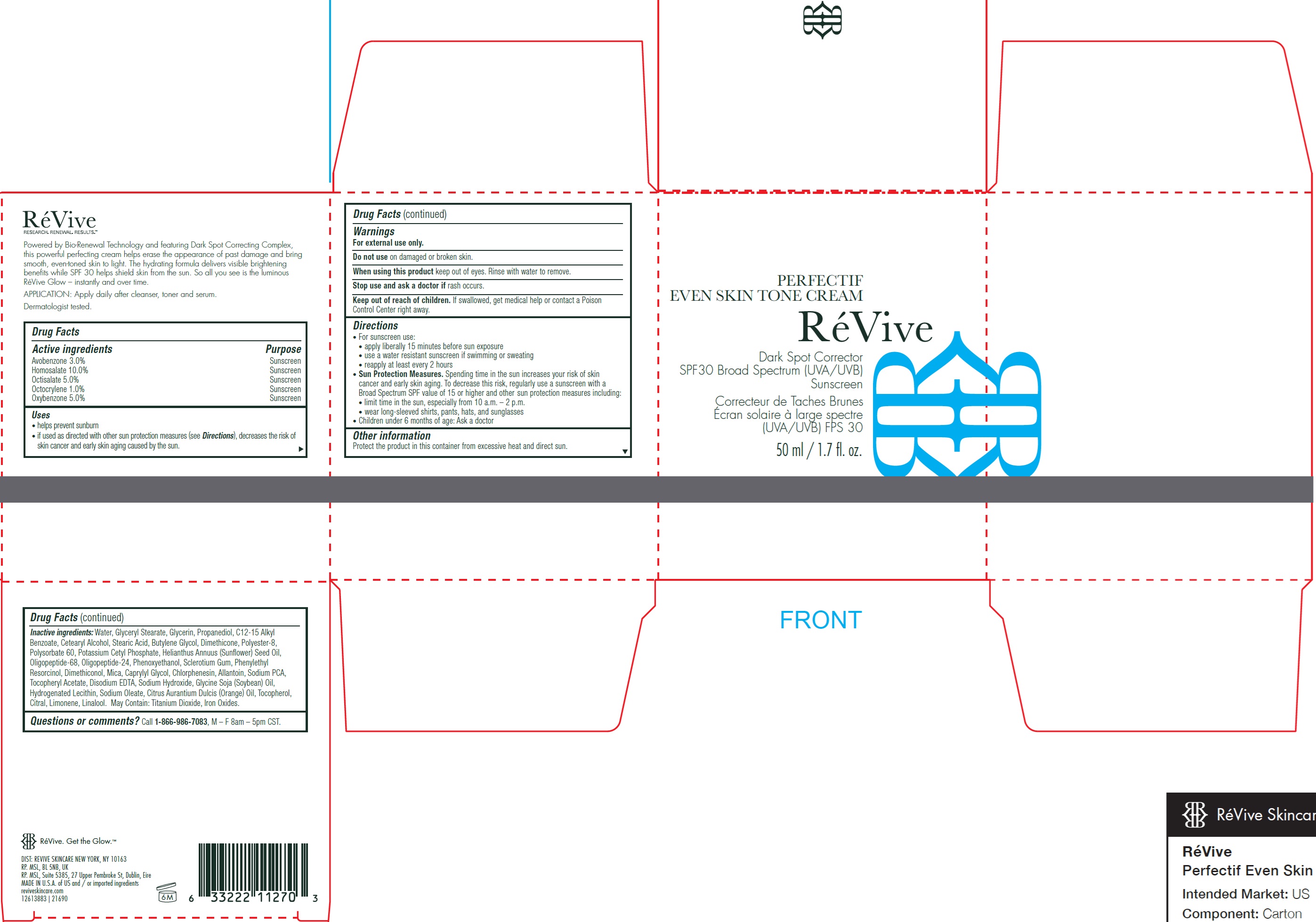 DRUG LABEL: Perfectif Even Skin Tone Cream Broad Spectrum SPF 30 Sunscreen
NDC: 82691-147 | Form: CREAM
Manufacturer: RV Skincare LLC
Category: otc | Type: HUMAN OTC DRUG LABEL
Date: 20260120

ACTIVE INGREDIENTS: AVOBENZONE 30 mg/1 mL; HOMOSALATE 100 mg/1 mL; OCTISALATE 50 mg/1 mL; OCTOCRYLENE 10 mg/1 mL; OXYBENZONE 50 mg/1 mL
INACTIVE INGREDIENTS: WATER; GLYCERYL MONOSTEARATE; GLYCERIN; PROPANEDIOL; ALKYL (C12-15) BENZOATE; CETOSTEARYL ALCOHOL; STEARIC ACID; BUTYLENE GLYCOL; DIMETHICONE; POLYSORBATE 60; POTASSIUM CETYL PHOSPHATE; SUNFLOWER OIL; PHENOXYETHANOL; BETASIZOFIRAN; PHENYLETHYL RESORCINOL; MICA; CAPRYLYL GLYCOL; CHLORPHENESIN; ALLANTOIN; SODIUM PYRROLIDONE CARBOXYLATE; .ALPHA.-TOCOPHEROL ACETATE; EDETATE DISODIUM ANHYDROUS; SODIUM HYDROXIDE; SOYBEAN OIL; SODIUM OLEATE; ORANGE OIL, COLD PRESSED; TOCOPHEROL; CITRAL; LIMONENE, (+)-; LINALOOL, (+/-)-; TITANIUM DIOXIDE; FERRIC OXIDE RED

Perfectif Even Skin Tone Cream Broad Spectrum SPF 30 Sunscreen

Active ingredients

Avobenzone 3.0%

Homosalate 10.0%

Octisalate 5.0%

Octocrylene 1.0%

Oxybenzone 5.0%

Purpose

Sunscreen

Uses

• helps prevent sunburn

• if used as directed with other sun protection measures (see), decreases the risk of skin cancer and early skin aging caused by the sun. Directions

Warnings

For external use only.

Do not use

on damaged or broken skin.

When using this product

keep out of eyes. Rinse with water to remove.

Stop use and ask a doctor if

rash occurs.

Keep out of reach of children.

If swallowed, get medical help or contact a Poison Control Center right away.

Directions

• For sunscreen use:

• apply liberally 15 minutes before sun exposure

• use a water resistant sunscreen if swimming or sweating

• reapply at least every 2 hours

• Sun Protection Measures.Spending time in the sun increases your risk of skin cancer and early skin aging. To decrease this risk, regularly use a sunscreen with a Broad Spectrum SPF value of 15 or higher and other sun protection measures including:

• limit time in the sun, especially from 10 a.m. – 2 p.m.

• wear long-sleeved shirts, pants, hats, and sunglasses

• Children under 6 months of age: Ask a doctor

Other information

Protect the product in this container from excessive heat and direct sun.

Inactive ingredients:

Water, Glyceryl Stearate, Glycerin, Propanediol, C12-15 Alkyl Benzoate, Cetearyl Alcohol, Stearic Acid, Butylene Glycol, Dimethicone, Polyester-8, Polysorbate 60, Potassium Cetyl Phosphate, Helianthus Annuus (Sunflower) Seed Oil, Oligopeptide-68, Oligopeptide-24, Phenoxyethanol, Sclerotium Gum, Phenylethyl Resorcinol, Dimethiconol, Mica, Caprylyl Glycol, Chlorphenesin, Allantoin, Sodium PCA, Tocopheryl Acetate, Disodium EDTA, Sodium Hydroxide, Glycine Soja (Soybean) Oil, Hydrogenated Lecithin, Sodium Oleate, Citrus Aurantium Dulcis (Orange) Oil, Tocopherol, Citral, Limonene, Linalool. May Contain: Titanium Dioxide, Iron Oxides.

Questions or comments?

Call , M – F 8am – 5pm CST. 1-866-986-7083